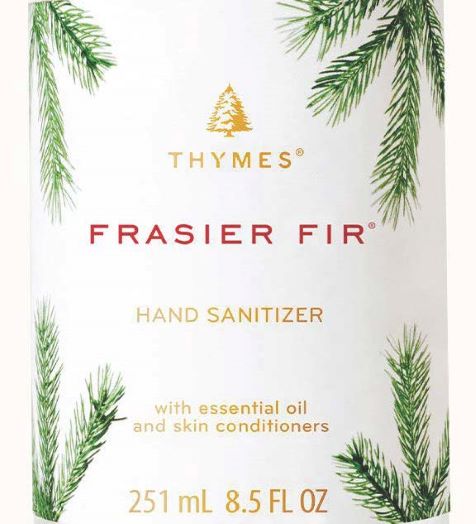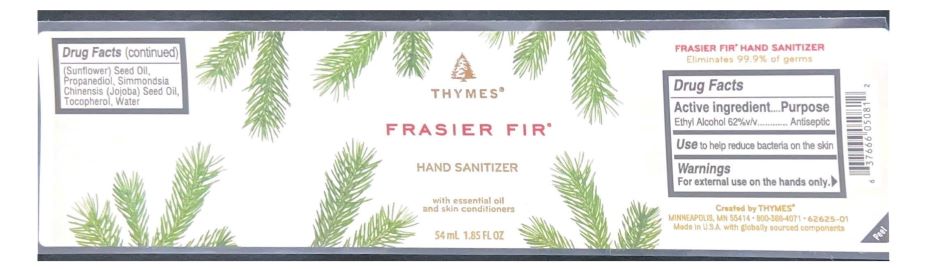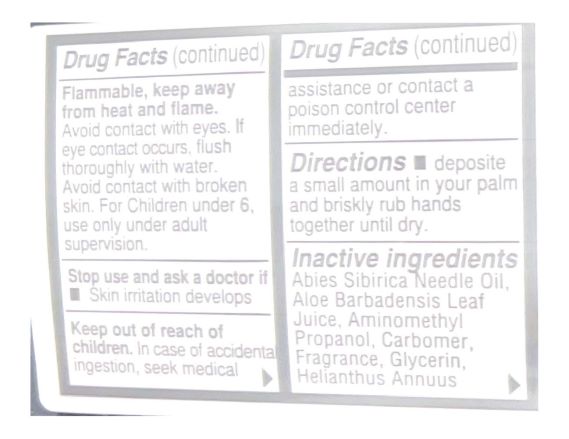 DRUG LABEL: Thymes Frasier Fir Hand Sanitizer
NDC: 76150-339 | Form: GEL
Manufacturer: Bell International Laboratories, Inc
Category: otc | Type: HUMAN OTC DRUG LABEL
Date: 20220408

ACTIVE INGREDIENTS: ALCOHOL 62 mL/100 mL
INACTIVE INGREDIENTS: TOCOPHEROL; WATER; GLYCERIN; ALOE VERA LEAF; JOJOBA OIL; PROPANEDIOL; SUNFLOWER OIL; CARBOMER HOMOPOLYMER, UNSPECIFIED TYPE; ABIES SIBIRICA LEAF OIL; AMINOMETHYLPROPANOL

Thymes Frasier Fir Hand Sanitizer

Active Ingredient

Ethyl Alcohol 62% v/v

Purpose

Antiseptic

Use

To help reduce bacteria on the skin

Warnings

Flammable, keep away from heat and flame. For external use on the hands only. Avoid contact with eyes. If eye contact occurs, flush thoroughly with water. Avoid contact with broken skin. For Children under 6, use only under adult supervision.

Stop use and ask a doctor if skin irritation develops

Keep out of reach of children. In case of accidental ingestion, seek medical assistance or contact a poison control center immediately.

Directions

Deposit a small amount in your palm and briskly rub hands together until dry.

Inactive Ingredients

Abies Sibirica Needle Oil, Aloe Barbadensis Leaf Juice, Aminomethyl Propanol, Carbomer, Fragrance, Glycerin, Helianthus Annuus (Sunflower) Seed Oil, Propanediol, Simmondsia Chinensis (Jojoba) Seed Oil, Tocopherol, Water